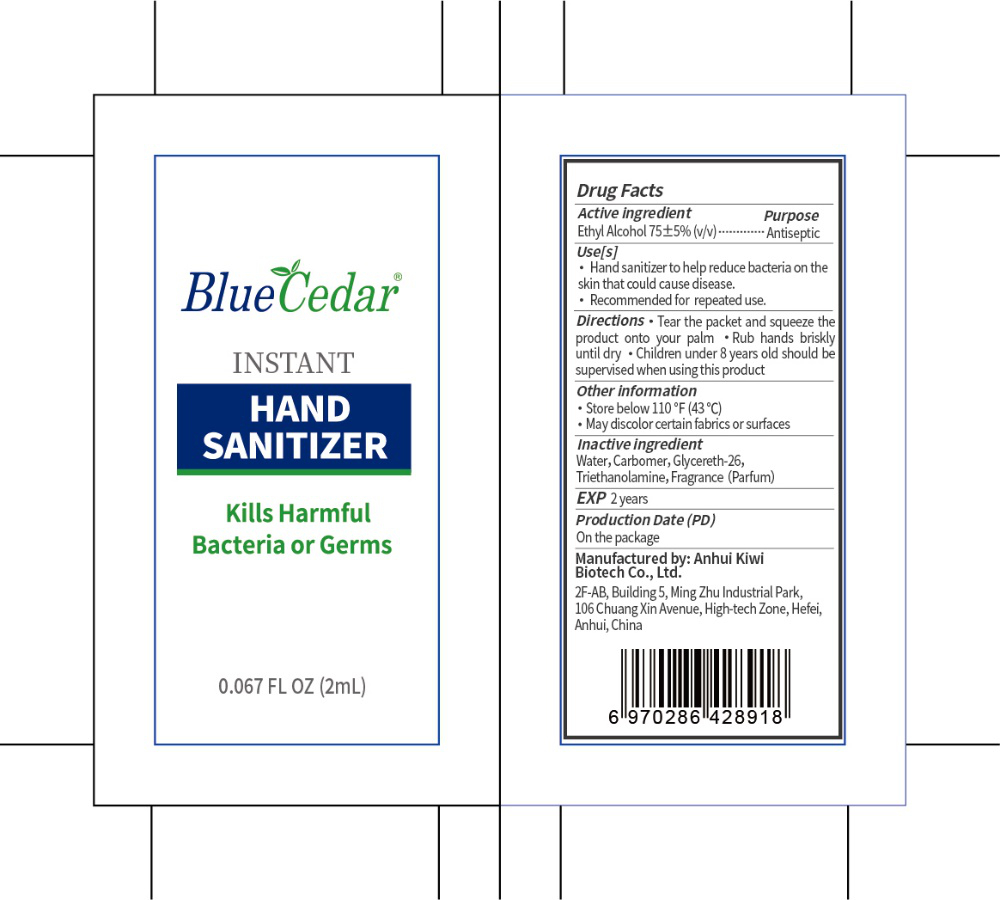 DRUG LABEL: Blue Cedar Hand Sanitizer
NDC: 55444-013 | Form: GEL
Manufacturer: Anhui Kiwi Biotech Co., Ltd.
Category: otc | Type: HUMAN OTC DRUG LABEL
Date: 20200706

ACTIVE INGREDIENTS: ALCOHOL 1.5 mL/2 mL
INACTIVE INGREDIENTS: GLYCERETH-26; TROLAMINE; FRAGRANCE LAVENDER & CHIA F-153480; WATER; CARBOMER HOMOPOLYMER, UNSPECIFIED TYPE

DOSAGE AND ADMINISTRATION

Store below 110 °F (43 °C).

INACTIVE INGREDIENT

Water, Carbomer, Glycereth-26, Triethanolamine, Fragrance(Parfum)

INDICATIONS AND USAGE

Place enough product (1.5-2 mL, about one full pump) in your palm to thoroughly cover your hands.Rub hands briskly until dry.

ACTIVE INGREDIENT

Ethyl Alcohol

keep out of reach of children

PURPOSE

Disinfection
Sterilization
No Rinseing

WARNINGS

Flammable. Keep away from fire or flame.For external use only.Do not use this product in or near the eyes. In case of accidental contact, rinse eyes thoroughly with water.